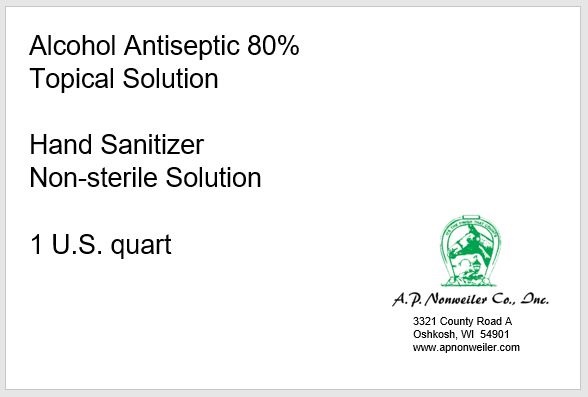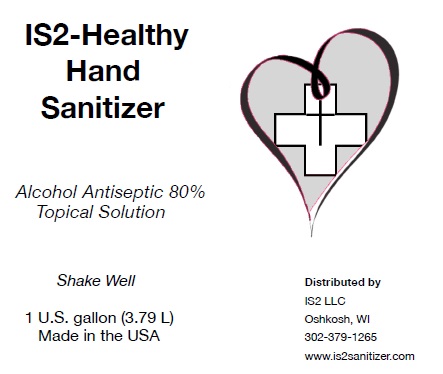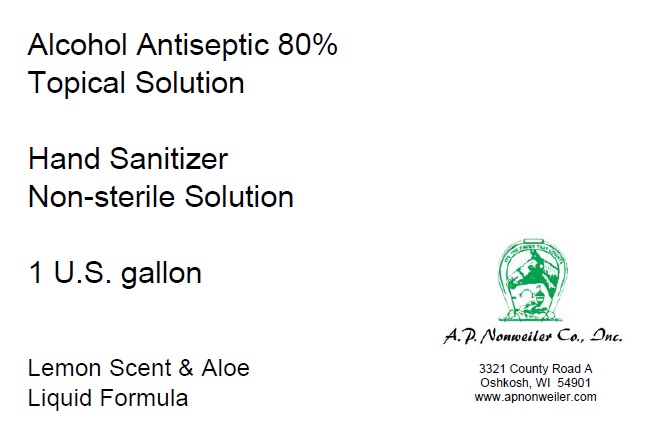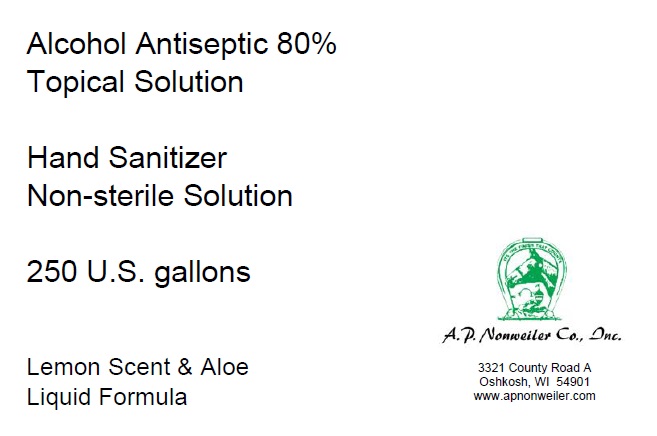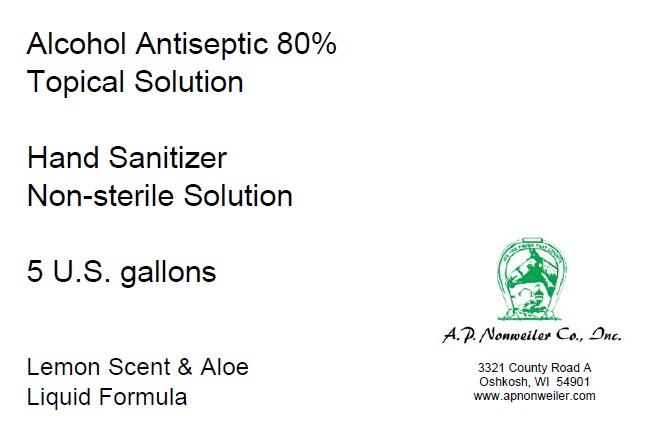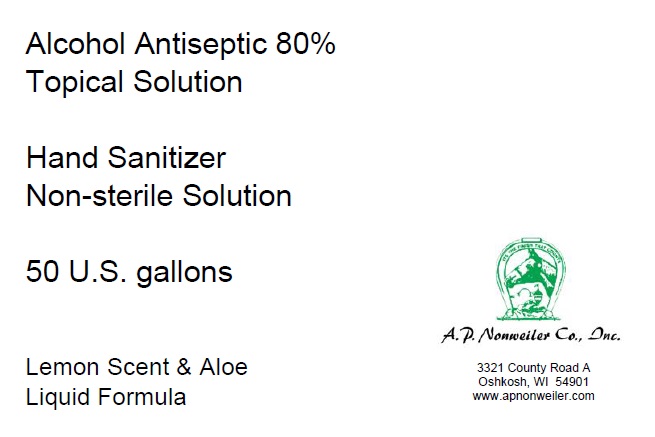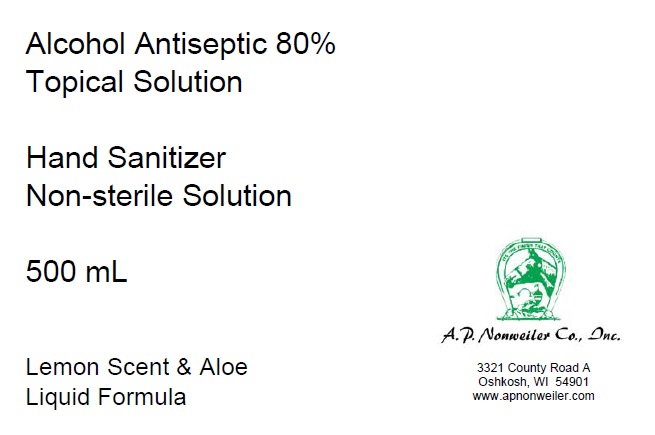 DRUG LABEL: Lewcizer 5
NDC: 74829-363 | Form: LIQUID
Manufacturer: A.P. Nonweiler Co., Inc.
Category: otc | Type: HUMAN OTC DRUG LABEL
Date: 20201120

ACTIVE INGREDIENTS: ALCOHOL 80.8 mL/100 mL
INACTIVE INGREDIENTS: ISOPROPYL ALCOHOL 4.1 mL/100 mL; ALOE VERA LEAF 1.8 mL/100 mL; CITRAL 0.1 mL/100 mL; HYDROGEN PEROXIDE 0.2 mL/100 mL; WATER

This is a hand sanitizer manufactured according to the Temporary Policy for Preparation of Certain Alcohol-Based Hand Sanitizer Products During the Public Health Emergency (CoViD-19); Guidance for Industry

Active Ingredient(s)

Alcohol 80% v/v. Purpose: Antiseptic

Purpose

Antiseptic, Hand Sanitizer

Use

Hand Sanitizer to help reduce bacteria that potentially can cause disease. For use when soap and water are not available.

Warnings

For external use only. Flammable. Keep away from heat or flame

Do not use

- in children less than 2 months of age
- on open skin wounds

When using this product keep out of eyes, ears, and mouth. In case of contact with eyes, rinse eyes thoroughly with water.
Stop use and ask a doctor if irritation or rash occurs. These may be signs of a serious condition.
Keep out of reach of children. If swallowed, get medical help or contact a Poison Control Center right away.

Stop use and ask a doctor if irritation or rash occurs. These may be signs of a serious condition.

Keep out of reach of children. If swallowed, get medical help or contact a Poison Control Center right away.

Directions

- Place enough product on hands to cover all surfaces. Rub hands together until dry.
- Supervise children under 6 years of age when using this product to avoid swallowing.

Other information

- Store between 15-30C (59-86F)
- Avoid freezing and excessive heat above 40C (104F)

Inactive ingredients

hydrogen peroxide, aloe vera gel, fragrance, sterile water

Package Label - Principal Display Panel

500 mL NDC: 74829-363-08

3785 mL NDC: 74829-363-01

946 mL NDC: 74829-363-04

18927 mL NDC: 74829-363-05

208197 mL NDC: 74829-363-50

1040988 mL NDC: 74829-363-25

3785 mL NDC: 74829-363-01IS2